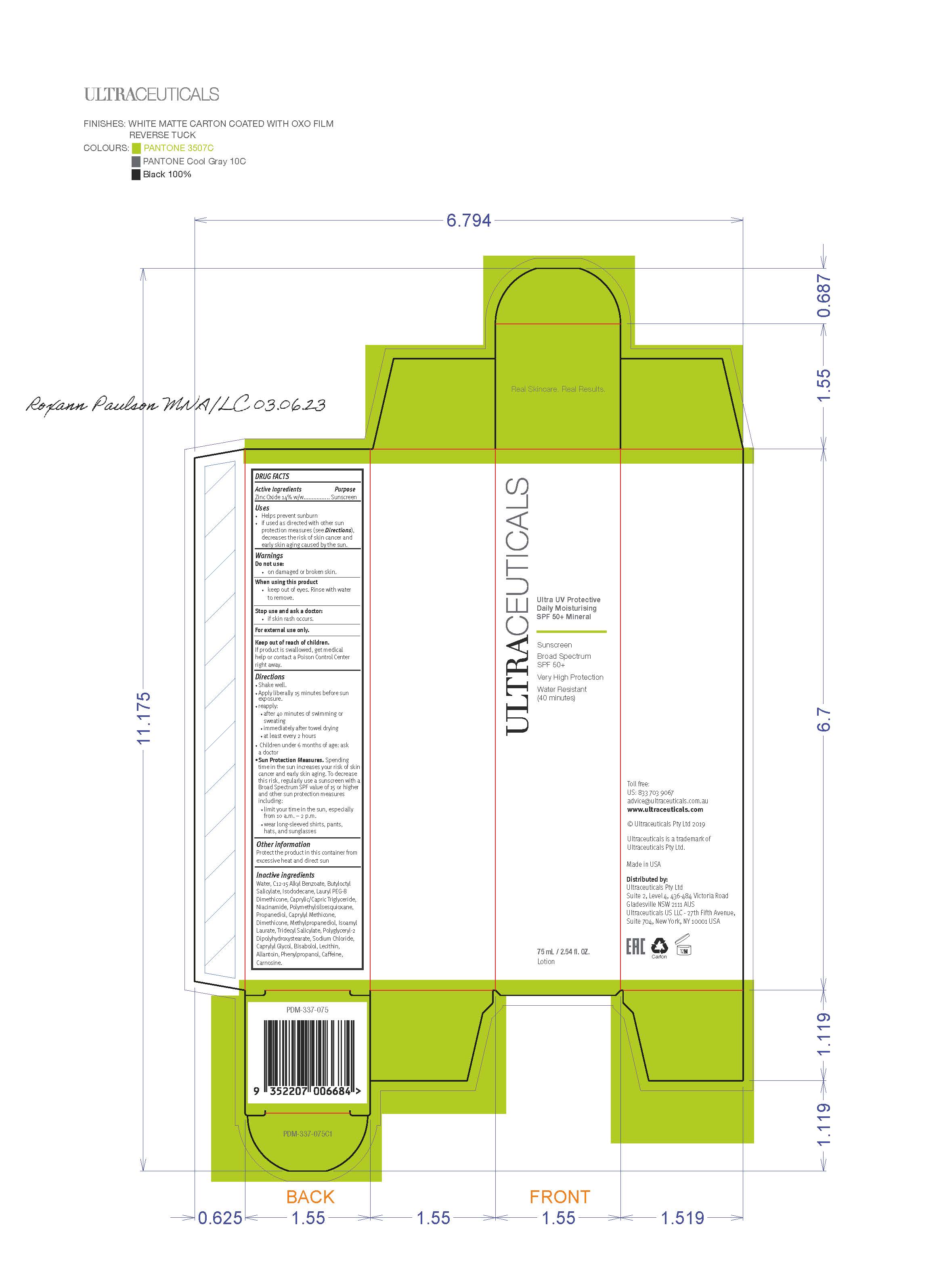 DRUG LABEL: Ultraceuticals Ultra UV Protective Daily Moisturising
NDC: 10028-158 | Form: LOTION
Manufacturer: Ultraceuticals
Category: otc | Type: HUMAN OTC DRUG LABEL
Date: 20251106

ACTIVE INGREDIENTS: ZINC OXIDE 154 mg/1 mL
INACTIVE INGREDIENTS: ALLANTOIN, (+)-; PHENYLPROPANOL; BUTYLOCTYL SALICYLATE; ISODODECANE; .ALPHA.-BISABOLOL, (+)-; WATER; NIACINAMIDE; GLYCERIN; PROPANEDIOL; SODIUM CHLORIDE; .BETA.-TOCOPHEROL; POLYMETHYLSILSESQUIOXANE (4.5 MICRONS); METHYLPROPANEDIOL; CAFFEINE; CARNOSINE; SILICON DIOXIDE; CAPRYLYL GLYCOL; TRIDECYL SALICYLATE; ISOAMYL LAURATE

Ultraceuticals Ultra UV Protective Daily Moisturising